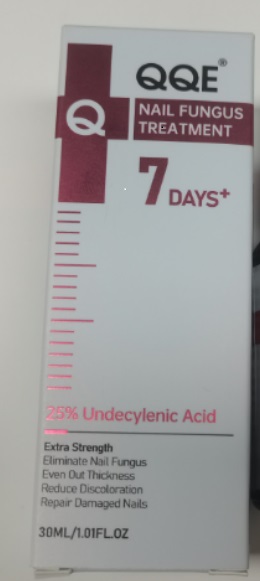 DRUG LABEL: QQE Nail Fungus Treatment
NDC: 84556-426 | Form: LIQUID
Manufacturer: Hainan Shengtaizhuo International Information Development Co., LTD
Category: otc | Type: HUMAN OTC DRUG LABEL
Date: 20251007

ACTIVE INGREDIENTS: UNDECYLENIC ACID 25 mg/30 g
INACTIVE INGREDIENTS: SIMMONDSIA CHINENSIS (JOJOBA) SEED OIL; CYCLOPENTASILOXANE; EUGENIA CARYOPHYLLUS (CLOVE) BUD OIL; LAVANDULA ANGUSTIFOLIA (LAVENDER) OIL; HELIANTHUS ANNUUS (SUNFLOWER) SEED OIL; TOCOPHEROL

ACTIVE INGREDIENT

Undecylenic Acid 25%

PURPOSE

Nail treatment

INDICATIONS AND USAGE

Apply the treatment to the affected area of the nails

WARNINGS

For external use only.For external use only Keep away from fire and flame

KEEP OUT OF REACH OF CHILDREN

If swallowed, get medical help or contact a Poison Control Center right away.

WHEN USING

1. Do not apply on other parts of the body
2. Avoid contact with the eyes in case of accidental contact rinse eyes with large arnounts of cool tap water.

DO NOT USE

You ae under 18 years of age, Do not use it on babies and children your scalp is red.inflamed.infected, irritated, or painful
You use other medicines .Ask a doctor before use if you hace heart disease.

STOP USE

Chest pain, rapid heart beat, faintness, or dizziness occurs sudden, unexplained weight gain occurs,your hands or feet swell.

DOSAGE AND ADMINISTRATION

Twice each day,4 sprays (1ml)each time. 15 days supply

INACTIVE INGREDIENT

Aloe Vera Extract, Helianthus Annuus (Sunflower) Seed Oil, Cyclopentasiloxane, Prunus Armeniaca (Apricot) Kernel Oil, Melaleuca Alternifolia (Tea Tree) Leaf Oil, Eugenia Caryophyllus (Clove) Bud Oil, Lavandula Angustifolia (Lavender) Oil, Hakka Yu, Tocopherol, Origanum Vulgare Oil, Simmondsia Chinensis (Jojoba) Seed Oil.